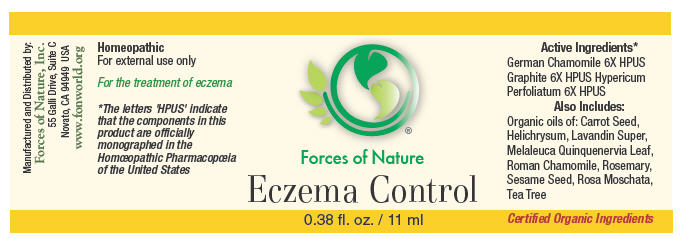 DRUG LABEL: Eczema Control
NDC: 51393-6222 | Form: SOLUTION/ DROPS
Manufacturer: Forces of Nature
Category: homeopathic | Type: HUMAN OTC DRUG LABEL
Date: 20100824

ACTIVE INGREDIENTS: Chamomile 6 [hp_X]/1000 mL; Graphite 6 [hp_X]/1000 mL; Hypericum Perforatum 6 [hp_X]/1000 mL
INACTIVE INGREDIENTS: Tea Tree Oil

Eczema Control

Drug Facts

Indications

For the treatment of eczema

ACTIVE INGREDIENT

PURPOSE

Homeopathic Active Ingredients [The letters 'HPUS' indicate that the components in this product are officially monographed in the Homœopathic Pharmacopœia of the United States.]
Equal parts of: | Purpose
Chamomilla 6X HPUS | To improve unhealthy skin
Graphites 6X HPUS | Relief from eczema, dry rough irritated skin
Hypericum 6X HPUS | For relief of eczema of face and hands

Also Contains

Certified Organic Oils of: Carrot Seed, Helichrysum, Lavandin Super, Melaleuca Quinquenervia Leaf Oil, Roman Chamomile, Rosemary, Sesame Seed, and Tea Tree, Rosa Moschata

Directions

Apply product directly to affected area and rub gently into the skin. Repeat 3 times per day. It may also help to apply a few drops to the soles of each foot 2-3 times per day, as well.

Warnings

Some individuals may be sensitive to essential oils. Begin with a small drop to determine if the product causes any increased redness or irritation and discontinue use if it irritates your skin.

PREGNANCY OR BREAST FEEDING

If you are pregnant or breast-feeding, ask a health professional before use.

WHEN USING

For external use only. If accidental ingestion more than several drops, and adverse reaction occurs, get medical help or contact a Poison Control Center. Do not apply to the eyes; in the event of contact, flush with water and seek advice from medical personnel.

KEEP OUT OF REACH OF CHILDREN

Not to be used with children under 2 years of age. Keep all medicines out of the reach of children.

Stop use and ask a doctor if condition worsens, symptoms last more than 7 days, or clear up and occur again within a few days.

Manufactured by:
Forces of Nature, Inc.
55 Galli Drive, Suite C
Novato, CA 94949 USA
www.fonworld.org

Product questions?

877-975-3797

NDC#: 51393-6222-1 (11ml) // 51393-6222-2 (33ml)

PRINCIPAL DISPLAY PANEL - 11 ml Bottle Label

Forces of Nature

Eczema Control

0.38 fl. oz. / 11 ml